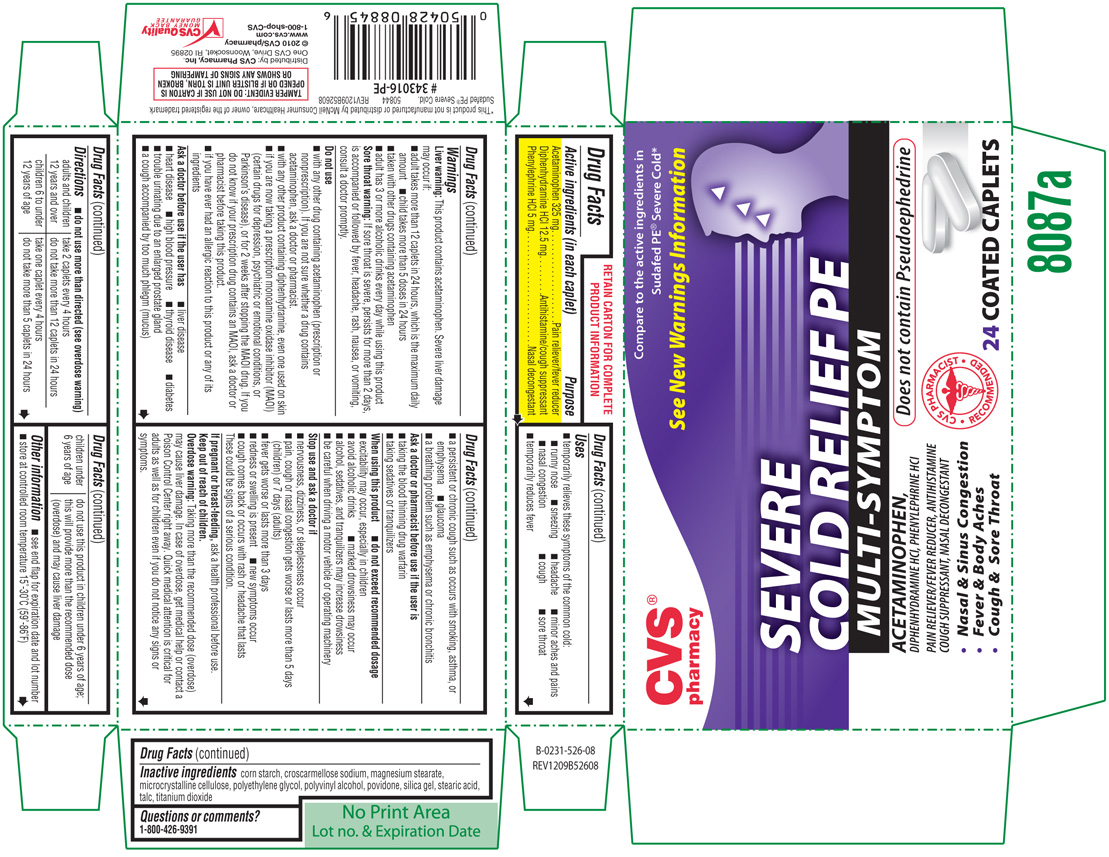 DRUG LABEL: Severe Cold Relief PE 
NDC: 59779-526 | Form: TABLET, FILM COATED
Manufacturer: WOONSOCKET PRESCRIPTION CENTER, INCORPORATED
Category: otc | Type: HUMAN OTC DRUG LABEL
Date: 20100826

ACTIVE INGREDIENTS: Acetaminophen 325 mg/1 1; Diphenhydramine Hydrochloride 12.5 mg/1 1; Phenylephrine Hydrochloride 5 mg/1 1
INACTIVE INGREDIENTS: Starch, Corn; Croscarmellose Sodium; Magnesium Stearate; Cellulose, Microcrystalline; Polyethylene Glycol; Polyvinyl Alcohol; Povidone; Silicon Dioxide; Stearic Acid; Talc; Titanium Dioxide

Active ingredients

(in each caplet)

Acetaminophen 325 mg

Diphenhydramine HCl 12.5 mg

Phenylephrine HCl 5 mg

Purpose

Pain reliever/fever reducer

Antihistamine/cough suppressant

Nasal decongestant

Uses

- temporarily relieves these symptoms of the common cold:
- runny nose
- sneezing
- headache
- minor aches and pains
- nasal congestion
- cough
- sore throat
- temporarily reduces fever

Warnings

Liver warning:

This product contains acetaminophen. Severe liver damage may occur if:

- adult takes more than 12 caplets in 24 hours, which is the maximum daily amount
- child takes more than 5 doses in 24 hours
- taking with other drugs containing acetaminophen
- adult has 3 or more alcoholic drinks every day while using this product

Sore throat warning:

If sore throat is severe, persists for more than 2 days, is accompanied or followed by fever, headache, rash, nausea, or vomiting, condult a doctor promptly.

Do not use

- with any other drug containing acetaminophen (prescription or nonprescription). If you are not sure whether a drug contains acetaminophen, ask a doctor or pharmacist.
- with any other product containing diphenhydramine, even one used on skin
- if you are now taking a prescription monoamine oxidase inhibitor (MAOI) (certain drugs for depression, psychiatric or emotional conditions, or Parkinson's disease), or for 2 weeks after stopping an MAOI, ask a doctor or pharmacist before taking this product.
- if you have ever had an allergic reaction to this product or any of its ingredients

Ask a doctor before use if the user has

- liver disease
- heart disease
- high blood pressure
- thyroid disease
- diabetes
- trouble urinating due to an enlarged prostate gland
- a cough accompanied by too much phlegm (mucus)
- a persistant or chronic cough such as occurs with smoking, asthma, or emphysema
- a breathing problem such as emphysema or chronic bronchitis

Ask a doctor or pharmacist before use if the user is

- taking the blood thinning drug warfarin
- taking sedatives or tranquilizers

When using this product

- do not exceed recommended dosage
- excitability may occur, especially in children
- avoid alcoholic drinks
- marked drowsiness may occur
- alcohol, sedatives, and tranquilizers may increase drowsiness
- be careful when driving a motor vehicle or operating machinery

Stop use and ask a doctor if

- nervousness, dizziness, or sleeplessness occur
- pain, cough or nasal congestion gets worse or lasts more than 5 days (children) or 7 days (adults)
- fever gets worse or lasts more than 3 days
- redness or swelling is present
- new symptoms occur
- cough comes back or occurs with rash or headache that lasts

These could be signs of a serious condition.

If pregnant or breast-feeding,

ask a health professional before use.

Keep out of reach of children.

Overdose warning: Taking more than the recommended dose (overdose) may cause liver damage. In case of overdose, get medical help or contact a Poison Control Centrer right away. Quick medical attention is critical for adults as well as for children even if you do not notice any signs or symptoms.

Directions

- do not use more than directed (see overdose warning)

adults and children 12 years and over | take 2 caplets every 4 hours; do not take more than 12 caplets in 24 hours
children 6 to under 12 years of age | take one caplet every 4 hours; do not take more than 5 caplets in 24 hours
children under 6 years of age | do not use this product in children under 6 years of age; this will provide more than the recommended dose (overdose) and may cause liver damage

Other information

- see end flap for expiration date and lot number
- store at controlled room temperature 15°-30°C (59°-86°F)

Inactive ingredients

corn starch, croscarmellose sodium, magnesium stearate, microcrystalline cellulose, polyethylene glycol, polyvinyl alcohol, povidone, silica gel, stearic acid, talc, titanium dioxide

Questions or comments?

1-800-426-9391

PRODUCT PACKAGING

The product packaging shown below represents a sample of that currently in use. Additional packaging may also be available.

CVS®

pharmacy

Compare to the active ingredients in

Sudafed PE® Severe Cold*

See New Warnings Information

SEVERE

COLD RELIEF PE

MULTI-SYMPTOM

ACETAMINOPHEN,

DIPHENHYDRAMINE HCl, PHENYLEPHRINE HCl

PAIN RELIEVER/FEVER REDUCER, ANTIHISTAMINE

COUGH SUPPRESSANT, NASAL DECONGESTANT

● Nasal & Sinus Congestion

● Fever & Body Aches

● Cough & Sore Throat

Does not contain Pseudoephedrine

24 COATED CAPLETS

TAMPER EVIDENT: DO NOT USE IF CARTON IS OPENED OR IF BLISTER UNIT IS TORN, BROKEN OR SHOWS ANY SIGNS OF TAMPERING

50844 REV1209B52608

Distributed by: CVS Pharmacy, Inc.

One CVS Drive, Woonsocket, RI 02895

© 2010 CVS/pharmacy

www.cvs.com

1-800-shop-CVS